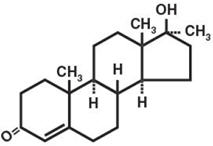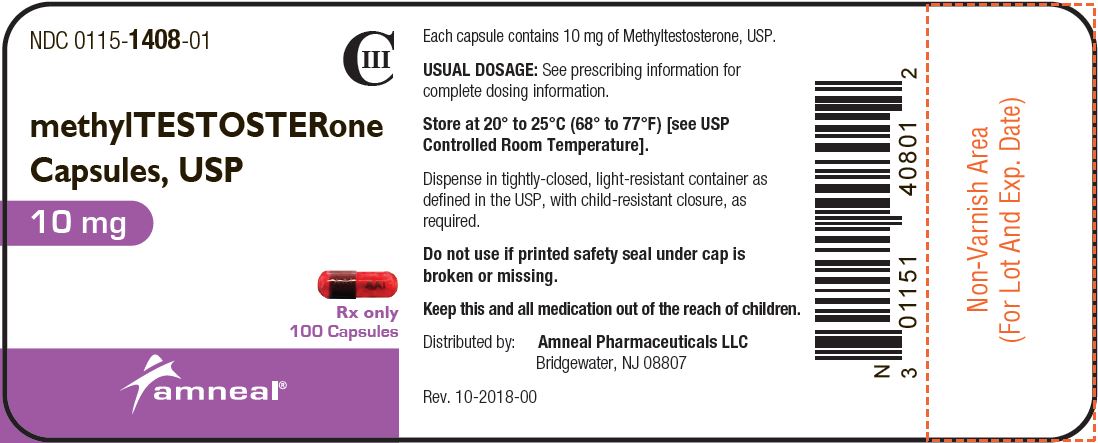 DRUG LABEL: MethylTESTOSTERone
NDC: 0115-1408 | Form: CAPSULE
Manufacturer: Amneal Pharmaceuticals of New York LLC
Category: prescription | Type: HUMAN PRESCRIPTION DRUG LABEL
Date: 20250531
DEA Schedule: CIII

ACTIVE INGREDIENTS: METHYLTESTOSTERONE 10 mg/1 1
INACTIVE INGREDIENTS: STARCH, CORN; D&C YELLOW NO. 10; GELATIN; FD&C BLUE NO. 1; FD&C BLUE NO. 2; FD&C RED NO. 40; FERROSOFERRIC OXIDE; MAGNESIUM STEARATE; PROPYLENE GLYCOL; SHELLAC

Methyltestosterone Capsules, USP, CIII
(10 mg)
Rx only

DESCRIPTION

The androgens are steroids that develop and maintain primary and secondary male sex characteristics.

Androgens are derivatives of cyclopentanoper-hydrophenanthrene. Endogenous androgens are C-19 steroids with a side chain at C-17, and with two angular methyl groups. Testosterone is the primary endogenous androgen. In their active form, all drugs in the class have a 17-beta hydroxy group. 17-alpha alkylation (methyltestosterone) increases the pharmacologic activity per unit weight compared to testosterone when given orally.

Methyltestosterone, a synthetic derivative of testosterone, is an androgenic preparation given by the oral route in a capsule form. It has the following structural formula:

C20H30O2 M.W. 302.46

17-β-hydroxy-17-methylandrost-4-en-3-one

Methyltestosterone, USP occurs as white or creamy white crystals or powder, which is soluble in various organic solvents but is practically insoluble in water.

Each capsule, for oral administration, contains 10 mg of methyltestosterone, USP. In addition, each capsule contains the following inactive ingredients: corn starch, D&C Yellow #10, gelatin, FD&C Blue #1, FD&C Red #40, and magnesium stearate. Additionally, the capsule printing inks contain D&C Yellow #10, FD&C Blue #1, FD&C Blue #2, FD&C Red #40, iron oxide black, propylene glycol, and shellac.

CLINICAL PHARMACOLOGY

Endogenous androgens are responsible for the normal growth and development of the male sex organs and for maintenance of secondary sex characteristics. These effects include the growth and maturation of prostate, seminal vesicles, penis, and scrotum. The development of male hair distribution, such as beard, pubic, chest, and axillary hair; laryngeal enlargement, vocal chord thickening, alterations in body musculature, and fat distribution. Drugs in this class also cause retention of nitrogen, sodium, potassium, phosphorus, and decreased urinary excretion of calcium. Androgens have been reported to increase protein anabolism and decrease protein catabolism. Nitrogen balance is improved only when there is sufficient intake of calories and protein.

Androgens are responsible for the growth spurt of adolescence and for the eventual termination of linear growth which is brought about by fusion of the epiphyseal growth centers. In children, exogenous androgens accelerate linear growth rates, but may cause a disproportionate advancement in bone maturation. Use over long periods may result in fusion of the epiphyseal growth centers and termination of growth process. Androgens have been reported to stimulate the production of red blood cells by enhancing the production of erythropoietic stimulating factor.

During exogenous administration of androgens, endogenous testosterone release is inhibited through feedback inhibition of pituitary luteinizing hormone (LH). At large doses of exogenous androgens, spermatogenesis may also be suppressed through feedback inhibition of pituitary follicle stimulating hormone (FSH).

There is a lack of substantial evidence that androgens are effective in fractures, surgery, convalescence and functional uterine bleeding.

Pharmacokinetics

Testosterone given orally is metabolized by the gut and 44 percent is cleared by the liver of the first pass. Oral doses as high as 400 mg per day are needed to achieve clinically effective blood levels for full replacement therapy. The synthetic androgen, methyltestosterone, is less extensively metabolized by the liver and has a longer half-life. It is more suitable than testosterone for oral administration.

Testosterone in plasma is 98 percent bound to a specific testosterone-estradiol binding globulin, and about 2 percent is free. Generally, the amount of this sex-hormone binding globulin in the plasma will determine the distribution of testosterone between free and bound forms, and the free testosterone concentration will determine its half-life.

About 90 percent of a dose of testosterone is excreted in the urine as glucuronic and sulfuric acid conjugates of testosterone and its metabolites; and 6 percent of a dose is excreted in the feces, mostly in the unconjugated form. Inactivation of testosterone occurs primarily in the liver. Testosterone is metabolized to various 17-keto steroids through two different pathways. There are considerable variations of the half-life of testosterone as reported in the literature, ranging from 10 to 100 minutes.

In many tissues the activity of testosterone appears to depend on reduction to dihydrotestosterone, which binds to cytosol receptor proteins. The steroid-receptor complex is transported to the nucleus where it initiates transcription events and cellular changes related to androgen action.

INDICATIONS AND USAGE

1. Males

Androgens are indicated for replacement therapy in conditions associated with a deficiency or absence of endogenous testosterone:

1. Primary hypogonadism (congenital or acquired) — testicular failure due to cryptorchidism, bilateral torsions, orchitis, vanishing testis syndrome; or orchidectomy.
2. Hypogonadotropic hypogonadism (congenital or acquired) — gonadotropin or luteinizing hormone-releasing hormone (LHRH) deficiency, or pituitary hypothalamic injury from tumors, trauma, or radiation. (Appropriate adrenal cortical and thyroid hormone replacement therapy are still necessary, however, and are actually of primary importance.) If the above conditions occur prior to puberty, androgen replacement therapy will be needed during the adolescent years for development of secondary sexual characteristics. Prolonged androgen treatment will be required to maintain sexual characteristics in these and other males who develop testosterone deficiency after puberty. Safety and efficacy of methyltestosterone in men with “age-related hypogonadism” (also referred to as “late-onset hypogonadism”) have not been established.
3. Androgens may be used to stimulate puberty in carefully selected males with clearly delayed puberty. These patients usually have a familial pattern of delayed puberty that is not secondary to a pathological disorder; puberty is expected to occur spontaneously at a relatively late date. Brief treatment with conservative doses may occasionally be justified in these patients if they do not respond to psychological support. The potential adverse effect on bone maturation should be discussed with the patient and parents prior to androgen administration. An X-ray of the hand and wrist to determine bone age should be obtained every 6 months to assess the effect of treatment on the epiphyseal centers (see WARNINGS).

2. Females

Androgens may be used secondarily in women with advancing inoperable metastatic (skeletal) mammary cancer who are 1 to 5 years postmenopausal. Primary goals of therapy in these women include ablation of the ovaries. Other methods of counteracting estrogen activity are adrenalectomy, hypophysectomy, and/or antiestrogen therapy. This treatment has also been used in premenopausal women with breast cancer who have benefitted from oophorectomy and are considered to have a hormone-responsive tumor. Judgment concerning androgen therapy should be made by an oncologist with expertise in this field.

CONTRAINDICATIONS

Androgens are contraindicated in men with carcinomas of the breast or with known or suspected carcinomas of the prostate, and in women who are or may become pregnant. When administered to pregnant women, androgens cause virilization of the external genitalia of the female fetus. This virilization includes clitoromegaly, abnormal vaginal development, and fusion of genital folds to form a scrotal-like structure. The degree of masculinization is related to the amount of drug given and the age of the fetus, and is most likely to occur in the female fetus when the drugs are given in the first trimester. If the patient becomes pregnant while taking these drugs, she should be apprised of the potential hazard to the fetus.

WARNINGS

In patients with breast cancer, androgen therapy may cause hypercalcemia by stimulating osteolysis. In this case, the drug should be discontinued.

Prolonged use of high doses of androgens has been associated with the development of peliosis hepatis and hepatic neoplasms including hepatocellular carcinoma (see PRECAUTIONS—Carcinogenesis). Peliosis hepatis can be a life-threatening or fatal complication.

Cholestatic hepatitis and jaundice occur with 17-alpha-alkylandrogens at a relatively low dose. If cholestatic hepatitis with jaundice appears or if liver function tests become abnormal, the androgen should be discontinued and the etiology should be determined. Drug-induced jaundice is reversible when the medication is discontinued.

Geriatric patients treated with androgens may be at an increased risk for the development of prostatic hypertrophy and prostatic carcinoma.

There have been postmarketing reports of venous thromboembolic events, including deep vein thrombosis (DVT) and pulmonary embolism (PE), in patients using testosterone products, such as methyltestosterone. Evaluate patients who report symptoms of pain, edema, warmth and erythema in the lower extremity for DVT and those who present with acute shortness of breath for PE. If a venous thromboembolic event is suspected, discontinue treatment with methyltestosterone and initiate appropriate workup and management.

Long term clinical safety trials have not been conducted to assess the cardiovascular outcomes of testosterone replacement therapy in men. To date, epidemiologic studies and randomized controlled trials have been inconclusive for determining the risk of major adverse cardiovascular events (MACE), such as non-fatal myocardial infarction, non-fatal stroke, and cardiovascular death, with the use of testosterone compared to non-use. Some studies, but not all, have reported an increased risk of MACE in association with use of testosterone replacement therapy in men. Patients should be informed of this possible risk when deciding whether to use or to continue to use methyltestosterone.

Testosterone can increase blood pressure which can increase cardiovascular (CV) risk over time. Monitor blood pressure periodically in men using testosterone products, especially in men with hypertension. Testosterone products are not recommended for use in patients with uncontrolled hypertension.

Testosterone has been subject to abuse, typically at doses higher than recommended for the approved indication and in combination with other anabolic androgenic steroids. Anabolic androgenic steroid abuse can lead to serious cardiovascular and psychiatric adverse reactions [see DRUG ABUSE AND DEPENDENCE].

If testosterone abuse is suspected, check serum testosterone concentrations to ensure they are within therapeutic range. However, testosterone levels may be in the normal or subnormal range in men abusing synthetic testosterone derivatives. Counsel patients concerning the serious adverse reactions associated with abuse of testosterone and anabolic androgenic steroids. Conversely, consider the possibility of testosterone and anabolic androgenic steroid abuse in suspected patients who present with serious cardiovascular or psychiatric adverse events.

Edema with or without congestive heart failure may be a serious complication in patients with preexisting cardiac, renal, or hepatic disease. In addition to discontinuation of the drug, diuretic therapy may be required.

Gynecomastia frequently develops and occasionally persists in patients being treated for hypogonadism.

Androgen therapy should be used cautiously in healthy males with delayed puberty. The effect on bone maturation should be monitored by assessing bone age of the wrist and hand every 6 months. In children, androgen treatment may accelerate bone maturation without producing compensatory gain in linear growth. This adverse effect may result in compromised adult stature. The younger the child the greater the risk of compromising final mature height.

This drug has not been shown to be safe and effective for the enhancement of athletic performance. Because of the potential risk of serious adverse health effects, this drug should not be used for such purpose.

PRECAUTIONS

General

Women should be observed for signs of virilization (deepening of the voice, hirsutism, acne, clitoromegaly and menstrual irregularities). Discontinuation of drug therapy at the time of evidence of mild virilism is necessary to prevent irreversible virilization. Such virilization is usual following androgen use at high doses. A decision may be made by the patient and the physician that some virilization will be tolerated during treatment for breast carcinoma.

Information for the Patient

The physician should instruct patients to report any of the following side effects of androgens:

Adult or Adolescent Males: | Too frequent or persistent erections of the penis. Any male adolescent patient receiving androgens for delayed puberty should have bone development checked every six months.
Women: | Hoarseness, acne, changes in menstrual periods or more hair on the face.
All Patients: | Any nausea, vomiting, changes in skin color or ankle swelling.

Laboratory Tests

1. Women with disseminated breast carcinoma should have frequent determination of urine and serum calcium levels during the course of androgen therapy (see WARNINGS).
2. Because of the hepatotoxicity associated with the use of 17-alpha-alkylated androgens, liver function tests should be obtained periodically.
3. Periodic (every 6 months) X-ray examinations of bone age should be made during treatment of prepubertal males to determine the rate of bone maturation and the effects of androgen therapy on the epiphyseal centers.
4. Hemoglobin and hematocrit should be checked periodically for polycythemia in patients who are receiving high doses of androgens.

Drug Interactions

1. Anticoagulants: C-17 substituted derivatives of testosterone, such as methandrostenolone, have been reported to decrease the anticoagulant requirements of
patients receiving oral anticoagulants. Patients receiving oral anticoagulant therapy require close monitoring, especially when androgens are started or stopped.
2. Oxyphenbutazone: Concurrent administration of oxyphenbutazone and androgens may result in elevated serum levels of oxyphenbutazone.
3. Insulin: In diabetic patients the metabolic effects of androgens may decrease blood glucose and insulin requirements.

Drug/Laboratory Test Interferences

Androgens may decrease levels of thyroxine-binding globulin, resulting in decreased total T4 serum levels and increased resin uptake of T3 and T4. Free thyroid hormone levels remain unchanged, however, and there is no clinical evidence of thyroid dysfunction.

Carcinogenesis

Animal Data

Testosterone has been tested by subcutaneous injection and implantation in mice and rats. The implant induced cervical-uterine tumors in mice, which metastasized in some cases. There is suggestive evidence that injection of testosterone into some strains of female mice increases their susceptibility to hepatoma. Testosterone is also known to increase the number of tumors and decrease the degree of differentiation of chemically induced carcinomas of the liver in rats.

Human Data

There are rare reports of hepatocellular carcinoma in patients receiving long-term therapy with androgens in high doses. Withdrawal of the drugs did not lead to regression of the tumors in all cases.

Geriatric patients treated with androgens may be at an increased risk for the development of prostatic hypertrophy and prostatic carcinoma.

Pregnancy

Teratogenic effects

Pregnancy Category X

(See CONTRAINDICATIONS).

Nursing Mothers

It is not known whether androgens are excreted in human milk. Because many drugs are excreted in human milk and because of the potential for serious adverse reactions in nursing infants from androgens, a decision should be made whether to discontinue nursing or to discontinue the drug, taking into account the importance of the drug to the mother.

Pediatric Use

Androgen therapy should be used very cautiously in children and only by specialists who are aware of the adverse effects on bone maturation. Skeletal maturation must be monitored every six months by an X-ray of hand and wrist (see INDICATIONS AND USAGE and WARNINGS).

ADVERSE REACTIONS

Endocrine and Urogenital

Female: The most common side effects of androgen therapy are amenorrhea and other menstrual irregularities, inhibition of gonadotropin secretion and virilization, including deepening of the voice and clitoral enlargement. The latter usually is not reversible after androgens are discontinued. When administered to a pregnant woman androgens cause virilization of external genitalia of the female fetus.

Male: Gynecomastia, and excessive frequency and duration of penile erections. Oligospermia may occur at high dosages (see CLINICAL PHARMACOLOGY).

Skin and appendages: Hirsutism, male pattern baldness, and acne.

Cardiovascular Disorders: myocardial infarction, stroke.

Fluid and Electrolyte Disturbances: Retention of sodium, chloride, water, potassium, calcium and inorganic phosphates.

Gastrointestinal: Nausea, cholestatic jaundice, alterations in liver function tests, rarely hepatocellular neoplasms and peliosis hepatis (see WARNINGS).

Hematologic: Suppression of clotting factors II, V, VII, and X, bleeding in patients on concomitant anticoagulant therapy and polycythemia.

Nervous System: Increased or decreased libido, headache, anxiety, depression, and generalized paresthesia.

Metabolic: Increased serum cholesterol.

Vascular Disorders: venous thromboembolism.

Miscellaneous: Rarely anaphylactoid reactions.

To report SUSPECTED ADVERSE REACTIONS, contact Amneal Pharmaceuticals at 1-877-835-5472 or FDA at 1-800-FDA-1088 or www.fda.gov/medwatch.

DRUG ABUSE AND DEPENDENCE

Controlled Substance

Methyltestosterone capsules contain testosterone, a Schedule III controlled substance in the Controlled Substances Act.

Abuse

Drug abuse is intentional non-therapeutic use of a drug, even once, for its rewarding psychological and physiological effects. Abuse and misuse of testosterone are seen in male and female adults and adolescents. Testosterone, often in combination with other anabolic androgenic steroids (AAS), and not obtained by prescription through a pharmacy, may be abused by athletes and bodybuilders. There have been reports of misuse by men taking higher doses of legally obtained testosterone than prescribed and continuing testosterone despite adverse events or against medical advice.

Abuse-Related Adverse Reactions

Serious adverse reactions have been reported in individuals who abuse anabolic androgenic steroids and include cardiac arrest, myocardial infarction, hypertrophic cardiomyopathy, congestive heart failure, cerebrovascular accident, hepatotoxicity, and serious psychiatric manifestations, including major depression, mania, paranoia, psychosis, delusions, hallucinations, hostility and aggression.

The following adverse reactions have also been reported in men: transient ischemic attacks, convulsions, hypomania, irritability, dyslipidemias, testicular atrophy, subfertility, and infertility.

The following additional adverse reactions have been reported in women: hirsutism, virilization, deepening of voice, clitoral enlargement, breast atrophy, male-pattern baldness, and menstrual irregularities.

The following adverse reactions have been reported in male and female adolescents: premature closure of bony epiphyses with termination of growth, and precocious puberty.

Because these reactions are reported voluntarily from a population of uncertain size and may include abuse of other agents, it is not always possible to reliably estimate their frequency or establish a causal relationship to drug exposure.

Dependence

Behaviors Associated with Addiction

Continued abuse of testosterone and other anabolic steroids, leading to addiction is characterized by the following behaviors:

- Taking greater dosages than prescribed
- Continued drug use despite medical and social problems due to drug use
- Spending significant time to obtain the drug when supplies of the drug are interrupted
- Giving a higher priority to drug use than other obligations
- Having difficulty in discontinuing the drug despite desires and attempts to do so
- Experiencing withdrawal symptoms upon abrupt discontinuation of use

Physical dependence is characterized by withdrawal symptoms after abrupt drug discontinuation or a significant dose reduction of a drug. Individuals taking supratherapeutic doses of testosterone may experience withdrawal symptoms lasting for weeks or months which include depressed mood, major depression, fatigue, craving, restlessness, irritability, anorexia, insomnia, decreased libido and hypogonadotropic hypodgonadism.

Drug dependence in individuals using approved doses of testosterone for approved indications has not been documented.

OVERDOSAGE

There have been no reports of acute overdosage with the androgens.

DOSAGE AND ADMINISTRATION

Prior to initiating methyltestosterone, confirm the diagnosis of hypogonadism by ensuring that serum testosterone concentrations have been measured in the morning on at least two separate days and that these serum testosterone concentrations are below the normal range.

Methyltestosterone capsules are administered orally. The suggested dosage for androgens varies depending on the age, sex, and diagnosis of the individual patient. Dosage is adjusted according to the patient’s response and the appearance of adverse reactions.

Replacement therapy in androgen-deficient males is 10 mg to 50 mg of methyltestosterone daily. Various dosage regimens have been used to induce pubertal changes in hypogonadal males, some experts have advocated lower dosages initially, gradually increasing the dose as puberty progresses with or without a decrease to maintenance levels. Other experts emphasize that higher dosages are needed to induce pubertal changes and lower dosages can be used for maintenance after puberty. The chronological and skeletal ages must be taken into consideration both in determining the initial dose and in adjusting the dose.

Doses used in delayed puberty generally are in the lower range of that given above, and for a limited duration, for example 4 to 6 months.

Women with metastatic breast carcinoma must be followed closely because androgen therapy occasionally appears to accelerate the disease. Thus, many experts prefer to use the shorter acting androgen preparations rather than those with prolonged activity for treating breast carcinoma, particularly during the early stages of androgen therapy. The dosage of methyltestosterone for androgen therapy in breast carcinoma in females is from 50 mg to 200 mg daily.

HOW SUPPLIED

Methyltestosterone Capsules USP, 10 mg are capsules with red translucent body and cap imprinted with “AA1” in black ink; containing white to off-white powder.
They are available as follows:

Bottles of 30: NDC 0115-1408-08
Bottles of 100: NDC 0115-1408-01
Bottles of 1000: NDC 0115-1408-03

Store at 20° to 25°C (68° to 77°F) [see USP Controlled Room Temperature]. Dispense in a tightly closed, light-resistant container as defined in the USP, with a child-resistant closure, as required.

Distributed by:
Amneal Pharmaceuticals LLC
Bridgewater, NJ 08807

Rev. 05-2025-01